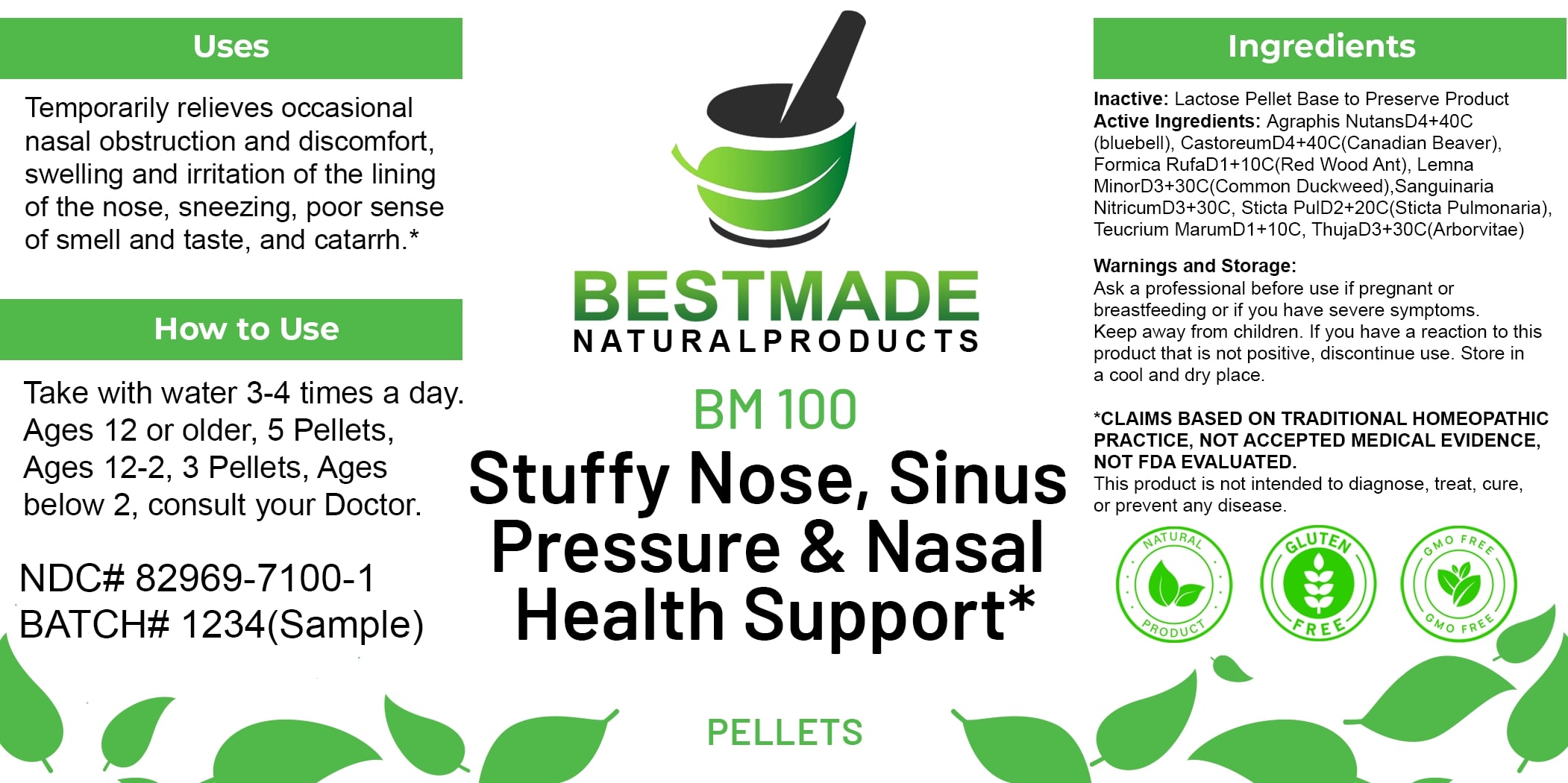 DRUG LABEL: Bestmade Natural Products BM100 Pellets
NDC: 82969-7100 | Form: TABLET, SOLUBLE
Manufacturer: Bestmade Natural Products
Category: homeopathic | Type: HUMAN OTC DRUG LABEL
Date: 20250408

ACTIVE INGREDIENTS: FORMICA RUFA 30 [hp_C]/30 [hp_C]; TEUCRIUM MARUM WHOLE 30 [hp_C]/30 [hp_C]; SANGUINARINE NITRATE 30 [hp_C]/30 [hp_C]; LOBARIA PULMONARIA 30 [hp_C]/30 [hp_C]; THUJA OCCIDENTALIS LEAFY TWIG 30 [hp_C]/30 [hp_C]; HYACINTHOIDES NON-SCRIPTA WHOLE 30 [hp_C]/30 [hp_C]; CASTOR FIBER SCENT GLAND SECRETION 30 [hp_C]/30 [hp_C]; LEMNA MINOR WHOLE 30 [hp_C]/30 [hp_C]
INACTIVE INGREDIENTS: LACTOSE 30 [hp_C]/30 [hp_C]

BM100 Pellets

DOSAGE AND ADMINISTRATION

How to Use

Take with water 3-4 times a day. Ages 12 or older, 5 Pellets, Ages 12-2, 3 Pellets, Ages below 2, consult your Doctor.

INACTIVE INGREDIENT

Ingredients

Inactive: Lactose Pellet Base to Preserve Product

ACTIVE INGREDIENT

Active Ingredients: Agraphis NutansD4+40C (Bluebell), CastoreumD4+40C(Canadian Beaver), Formica RufaD1+10C(Red Wood Ant), Lemna MinorD3+30C(Common Duckweed), Sanguinaria NitricumD3+30C, Sticta PulD2+20C(Sticta Pulmonaria), Teucrium MarumD1+10C, ThujaD3+30C(Arborvitae)

Uses

Temporarily relieves occasional nasal obstruction and discomfort, swelling and irritation of the lining of the nose, sneezing, poor sense
of smell and taste, and catarrh.*

*CLAIMS BASED ON TRADITIONAL HOMEOPATHIC PRACTICE. NOT ACCEPTED MEDICAL EVIDENCE. NOT FDA EVALUATED.

This product is not intended to diagnose, treat, cure, or prevent any disease.

Uses

Temporarily relieves occasional nasal obstruction and discomfort, swelling and irritation of the lining of the nose, sneezing, poor sense
of smell and taste, and catarrh.*

*CLAIMS BASED ON TRADITIONAL HOMEOPATHIC PRACTICE. NOT ACCEPTED MEDICAL EVIDENCE. NOT FDA EVALUATED.

This product is not intended to diagnose, treat, cure, or prevent any disease.

KEEP OUT OF REACH OF CHILDREN

Warnings and Storage:

Ask a professional before use if pregnant or breastfeeding or if you have severe symptoms. Keep away from children. If you have a reaction to this product that is not positive, discontinue use. Store in a cool and dry place.

Warnings and Storage:

Ask a professional before use if pregnant or breastfeeding or if you have severe symptoms. Keep away from children. If you have a reaction to this product that is not positive, discontinue use. Store in a cool and dry place.

*CLAIMS BASED ON TRADITIONAL HOMEOPATHIC PRACTICE. NOT ACCEPTED MEDICAL EVIDENCE. NOT FDA EVALUATED.

This product is not intended to diagnose, treat, cure, or prevent any disease.

Entire package label